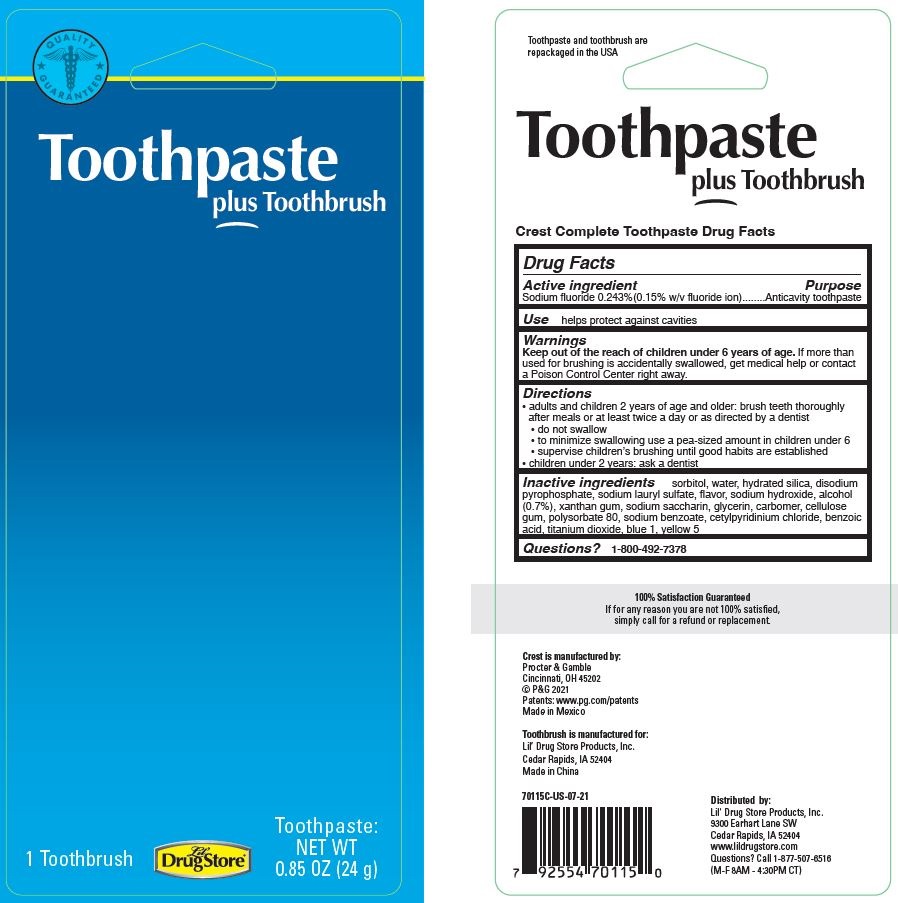 DRUG LABEL: Toothpaste, plus Toothbrush
NDC: 66715-7011 | Form: KIT | Route: DENTAL
Manufacturer: Lil' Drug Store Products, Inc.
Category: otc | Type: HUMAN OTC DRUG LABEL
Date: 20240409

ACTIVE INGREDIENTS: SODIUM FLUORIDE 1.5 mg/1 g
INACTIVE INGREDIENTS: FD&C YELLOW NO. 5; HYDRATED SILICA; GLYCERIN; XANTHAN GUM; SODIUM BENZOATE; BENZOIC ACID; FD&C BLUE NO. 1; TITANIUM DIOXIDE; POLYSORBATE 80; SODIUM ACID PYROPHOSPHATE; SODIUM HYDROXIDE; SACCHARIN SODIUM; CETYLPYRIDINIUM CHLORIDE; CARBOXYMETHYLCELLULOSE SODIUM; SORBITOL; ALCOHOL; WATER; SODIUM LAURYL SULFATE

Toothbrush & Toothpaste Kit, Lil' Drug Store®

Active ingredient

Sodium fluoride 0.243%(0.15% w/v fluoride ion)

Purpose

Anticavity toothpaste

Use

helps protect against cavities

Warnings

Keep out of the reach of children under 6 years of age. If more than used for brushing is accidentally swallowed, get medical help or contact a Poison Control Center right away.

Directions

- adults and children 2 years of age and older: brush teeth thoroughly after meals or at least twice a day or as directed by a dentist
- do not swallow
- to minimize swallowing use a pea-sized amount in children under 6
- supervise children’s brushing until good habits are established
- children under 2 years: ask a dentist

Inactive ingredients

sorbitol, water, hydrated silica, disodium pyrophosphate, sodium lauryl sulfate, flavor, sodium hydroxide, alcohol (0.7%), xanthan gum, sodium saccharin, glycerin, carbomer, cellulose gum, polysorbate 80, sodium benzoate, cetylpyridinium chloride, benzoic acid, titanium dioxide, blue 1, yellow 5

Questions?

1-800-492-7378

Toothpaste plus Toothbrush, Lil' Drug Store - PDP/Package

[caduceus]

Toothpaste

plus Toothbrush

1 Toothbrush

[Lil' Drug Store® logo]

Toothpaste:

NET WT

0.85 OZ (24 g)